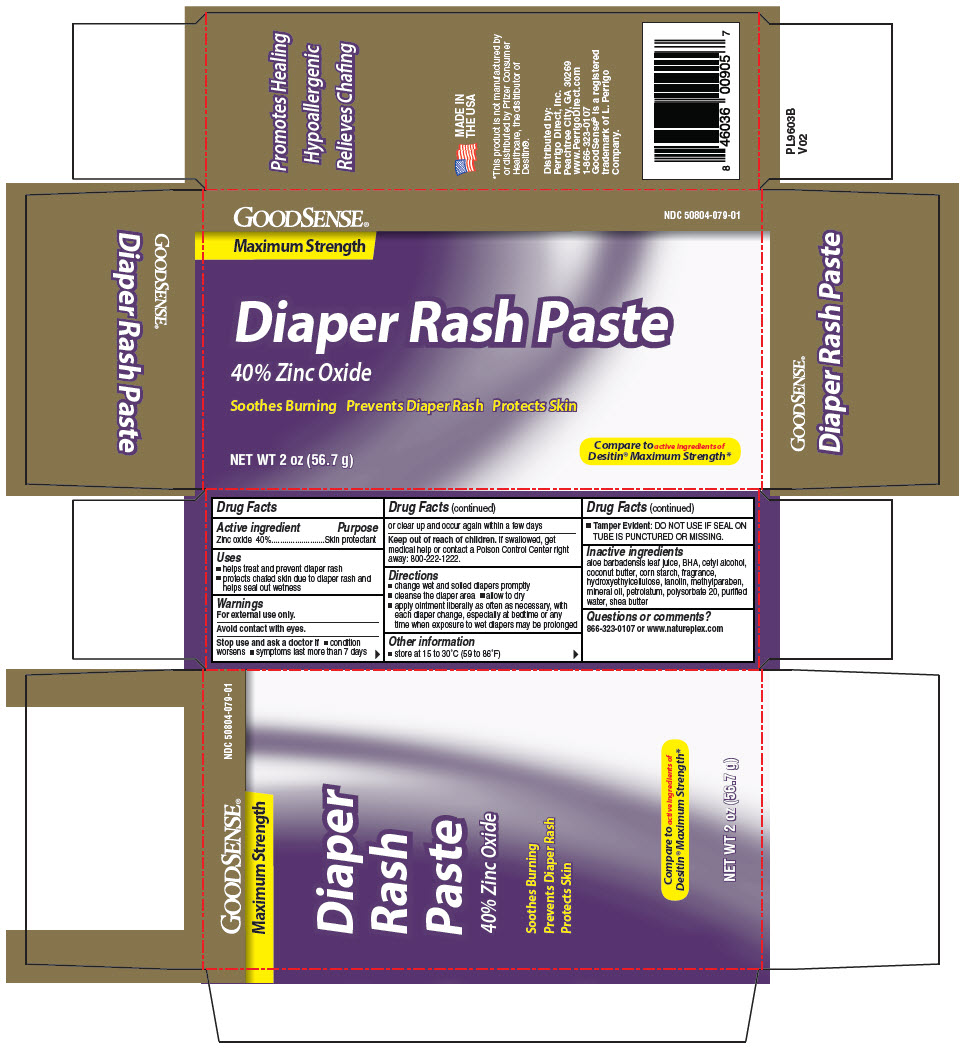 DRUG LABEL: Diaper Rash
NDC: 50804-079 | Form: PASTE
Manufacturer: GOODSENSE
Category: otc | Type: HUMAN OTC DRUG LABEL
Date: 20220317

ACTIVE INGREDIENTS: Zinc Oxide 400 mg/1 g
INACTIVE INGREDIENTS: Aloe Vera Leaf; Butylated Hydroxyanisole; Cetyl Alcohol; Cocoa Butter; Starch, Corn; Hydroxyethyl Cellulose, Unspecified; Lanolin; Methylparaben; Mineral Oil; Petrolatum; Polysorbate 20; Water; Shea Butter

Diaper Rash Paste

Drug Facts

Active ingredient

Zinc oxide 40%

Purpose

Skin protectant

Uses

- helps treat and prevent diaper rash
- protects chafed skin due to diaper rash and helps seal out wetness

Warnings

For external use only.

Avoid contact with eyes.

Stop use and ask a doctor if

- condition worsens
- symptoms last more than 7 days or clear up and occur again within a few days

Keep out of reach of children. If swallowed, get medical help or contact a Poison Control Center right away: 800-222-1222.

Directions

- change wet and soiled diapers promptly
- cleanse the diaper area
- allow to dry
- apply ointment liberally as often as necessary, with each diaper change, especially at bedtime or any time when exposure to wet diapers may be prolonged

Other information

- store at 15 to 30°C (59 to 86°F)
- Tamper Evident: DO NOT USE IF SEAL ON TUBE IS PUNCTURED OR MISSING.

Inactive ingredients

aloe barbadensis leaf juice, BHA, cetyl alcohol, coconut butter, corn starch, fragrance, hydroxyethylcellulose, lanolin, methylparaben, mineral oil, petrolatum, polysorbate 20, purified water, shea butter

Questions or comments?

866-323-0107 or www.natureplex.com

Distributed by:
Perrigo Direct, Inc.
Peachtree City, GA 30269

PRINCIPAL DISPLAY PANEL - 56.7 g Tube Carton

GOODSENSE®
NDC 50804-079-01

Maximum Strength

Diaper Rash Paste

40% Zinc Oxide

Soothes Burning
Prevents Diaper Rash
Protects Skin

NET WT 2 oz (56.7 g)

Compare to active ingredients of
Desitin® Maximum Strength*